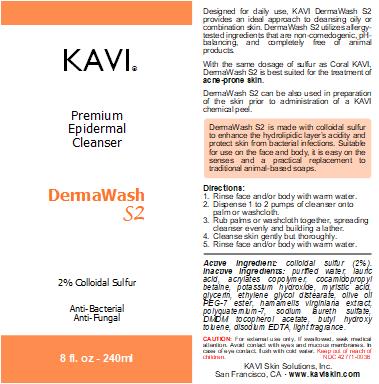 DRUG LABEL: DermaWash S2
NDC: 42771-0036 | Form: SOAP
Manufacturer: KAVI Skin Solutions, Inc.
Category: otc | Type: HUMAN OTC DRUG LABEL
Date: 20201020

ACTIVE INGREDIENTS: SULFUR 2 g/100 g
INACTIVE INGREDIENTS: TROLAMINE 7 g/100 g; GLYCOL DISTEARATE 3 g/100 g; SODIUM LAURETH SULFATE 3 g/100 g; MYRISTIC ACID 2 g/100 g; LAURYL BETAINE 2 g/100 g; WATER 57.75 g/100 g; SODIUM LAURYL SULFATE 10 g/100 g

DermaWash S2

Dosage & Administration

Directions for Use:
1. Rinse face and/or body with warm water.
2. Dispense 1 to 2 pumps of cleanser onto palm or washcloth.
3. Rub palms or washcloth together, spreading cleanser evenly and building a lather.
4. Cleanse skin gently but thoroughly.
5. Rinse face and/or body with warm water.

Purpose

Designed for daily use, KAVI DermaWash S2 provides an ideal approach to cleansing oily or combination skin. DermaWash S2 utilizes allergy-tested ingredients that are non-comedogenic, pH-balancing, and completely free of animal products.

With the same dosage of sulfur as Coral KAVI, DermaWash S2 is best suited for the treatment of acne-prone skin.
DermaWash S2 can be also used in preparation of the skin prior to administration of a KAVI chemical peel.

Indications & Usage

DermaWash S2 is best suited for the treatment of acne-prone skin.

Directions:
1. Rinse face and/or body with warm water.
2. Dispense 1 to 2 pumps of cleanser onto palm or washcloth.
3. Rub palms or washcloth together, spreading cleanser evenly and building a lather.
4. Cleanse skin gently but thoroughly.
5. Rinse face and/or body with warm water.

Active Ingredients

Active Ingredient: colloidal sulfur (2%)

Inactive Ingredients

Inactive Ingredients: purified water, lauric acid, acrylates copolymer, cocamidopropyl betaine, potassium hydroxide, myristic acid, glycerin, ethylene glycol distearate, olive oil PEG-7 ester, hamamelis virginiana extract, polyquaternium-7, sodium laureth sulfate, DMDM tocopherol acetate, butyl hydroxy toluene, disodium EDTA, light fragrance.

Warnings

For external use only. If swallowed, seek medical attention. Avoid contact with eyes and mucous membranes. In case of eye contact, flush with cold water. Keep out of reach of children.

Keep out of reach of children

CAUTION: For external use only. If swallowed, seek medical attention. Avoid contact with eyes and mucous membranes. In case of eye contact, flush with cold water. Keep out of reach of children.

Front and Back Labels

Designed for daily use, KAVI DermaWash S2 provides an ideal approach to cleansing oily or combination skin. DermaWash S2 utilizes allergy-tested ingredients that are non-comedogenic, pH-balancing, and completely free of animal products.
With the same dosage of sulfur as Coral KAVI, DermaWash S2 is best suited for the treatment of acne-prone skin.
DermaWash S2 can be also used in preparation of the skin prior to administration of a KAVI chemical peel.

DermaWash S2 is made with colloidal sulfur to enhance the hydrolipidic layer’s acidity and protect skin from bacterial infections. Suitable for use on the face and body, it is easy on the senses and a practical replacement to traditional animal-based soaps.

Directions:
1. Rinse face and/or body with warm water.
2. Dispense 1 to 2 pumps of cleanser onto palm or washcloth.
3. Rub palms or washcloth together, spreading cleanser evenly and building a lather.
4. Cleanse skin gently but thoroughly.
5. Rinse face and/or body with warm water.

Active Ingredient: colloidal sulfur (2%). Inactive Ingredients: purified water, lauric acid, acrylates copolymer, cocamidopropyl betaine, potassium hydroxide, myristic acid, glycerin, ethylene glycol distearate, olive oil PEG-7 ester, hamamelis virginiana extract, polyquaternium-7, sodium laureth sulfate, DMDM tocopherol acetate, butyl hydroxy toluene, disodium EDTA, light fragrance.

CAUTION: For external use only. If swallowed, seek medical attention. Avoid contact with eyes and mucous membranes. In case of eye contact, flush with cold water. Keep out of reach of children.